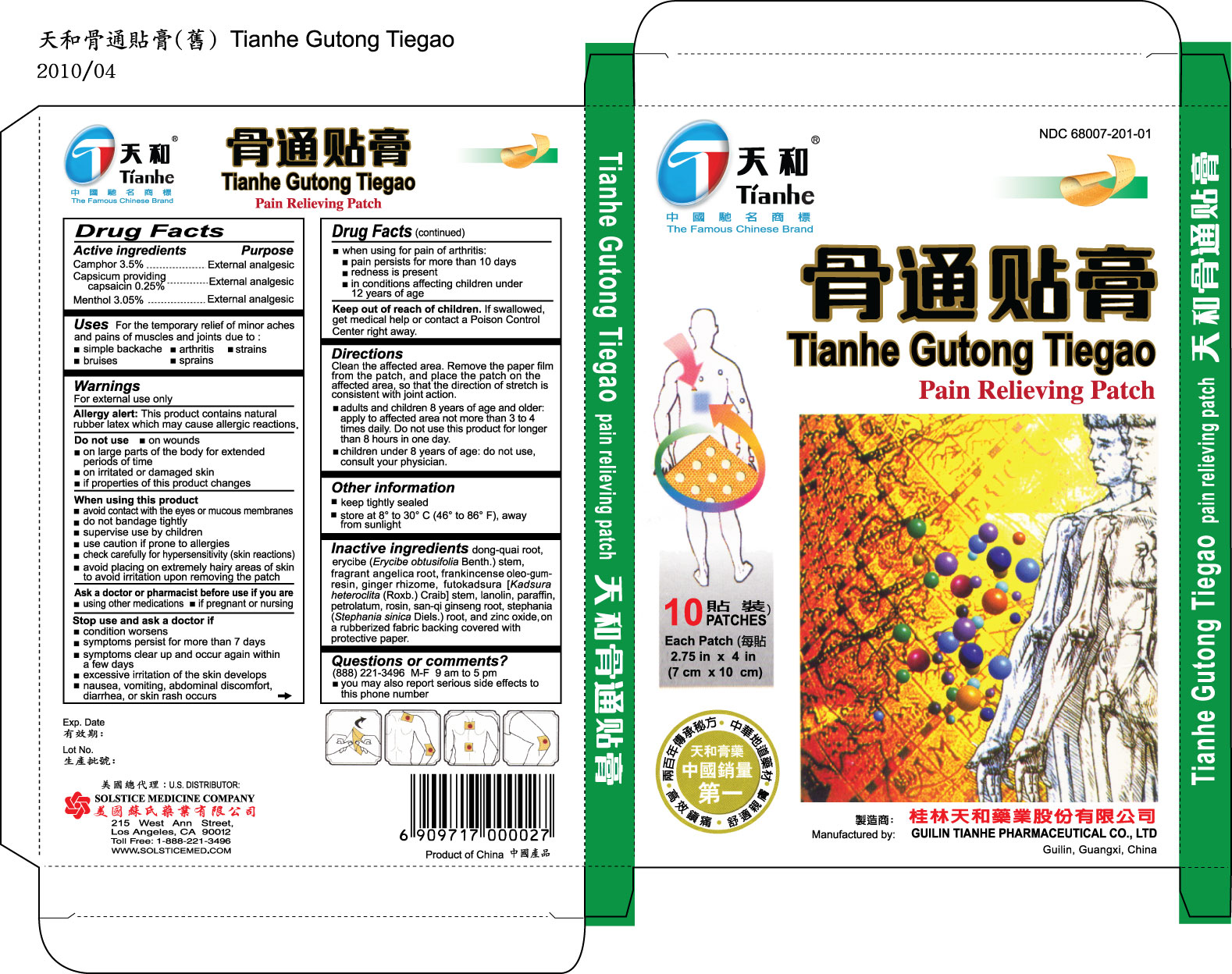 DRUG LABEL: TIANHE GUTONG TIEGAO
NDC: 68007-201 | Form: PATCH
Manufacturer: GUILIN TIANHE PHARMACEUTICAL CO LTD
Category: otc | Type: HUMAN OTC DRUG LABEL
Date: 20100524

ACTIVE INGREDIENTS: CAMPHOR (NATURAL) 3.5 g/1 1; CAPSAICIN 0.25 g/1 1; MENTHOL 3.05 g/1 1

DRUG FACTS

Active ingredients

Camphor 3.5%

Capsicum providing capsaicin 0.25%

Menthol 3.05%

Purpose External analgesic

Uses For the temporary relief of minor aches and pains of muscles and joints due to:

- simple backache
- arthritis
- strains
- bruises
- sprains

Do not use

- on wounds
- on large parts of the body for extended periods of time
- on irritated or damaged skin
- if properties of this product changes

When using this product

- avoid contact with the eyes or mucous membranes
- do not bandage tightly
- supervise use by children
- use caution if prone to allergies
- check carefully for hypersensitivity (skin reactions)
- avoid placing on extremely hairy areas of skin to avoid irritation upon removing the patch

Ask a doctor or pharmacist before use if you are

- using other medications
- if pregnant or nursing

Stop use and ask a doctor if

- condition worsens
- symptoms persist for more than 7 days
- symptoms clear up and occur again within a few days
- excessive irritation of the skin develops
- nausea, vomiting, abdominal discomfort, diarrhea, or skin rash occurs
- when using for pain of arthritis:
-
  - pain persists for more than 10 days
  - redness is present
  - in conditions affecting children under 12 years of age

Keep out of reach of children. If swallowed, get medical help or contact a
Poison Control Center right away.

DOSAGE AND ADMINISTRATION

Directions Clean the affected area. Remove the paper film from the patch,and place the patch on the affected area, so that the direction of stretch is consistent with joint action.

- adults and children 8 years of age and older: apply to affected area not more than 3 to 4 times daily. Do not use this product for longer than 8 hours in one day.
- children under 8 years of age: do not use, consult your physician.

Other information

- keep tightly sealed
- store at 8º to 30º C (46º to 86º F), away from sunlight

INACTIVE INGREDIENT

Inactive ingredients dong-quai root, erycibe (Erycibe obtusifolia Benth.)
stem, fragrant angelica root, frankincense oleo-gum-resin, ginger rhizome,
futokadsura [Kadsura heteroclita (Roxb.) Craib] stem, lanolin, paraffin,
petrolatum, rosin, san-qi ginseng root, stephania (Stephania sinica Diels.) root,
and zinc oxide, on a rubberized fabric backing covered with protective paper.

Questions or comments? (888) 221-3496 M-F 9 am to 5 pm

- you may also report serious side effects to this phone number

PACKAGE LABEL

TIANHE GUTONG TIEGAO PAIN RELIEVING PATCH NDC 68007-201-01 10 PATCHES EACH PATCH 2.75 IN X 4 IN (7 CM X 10 CM)